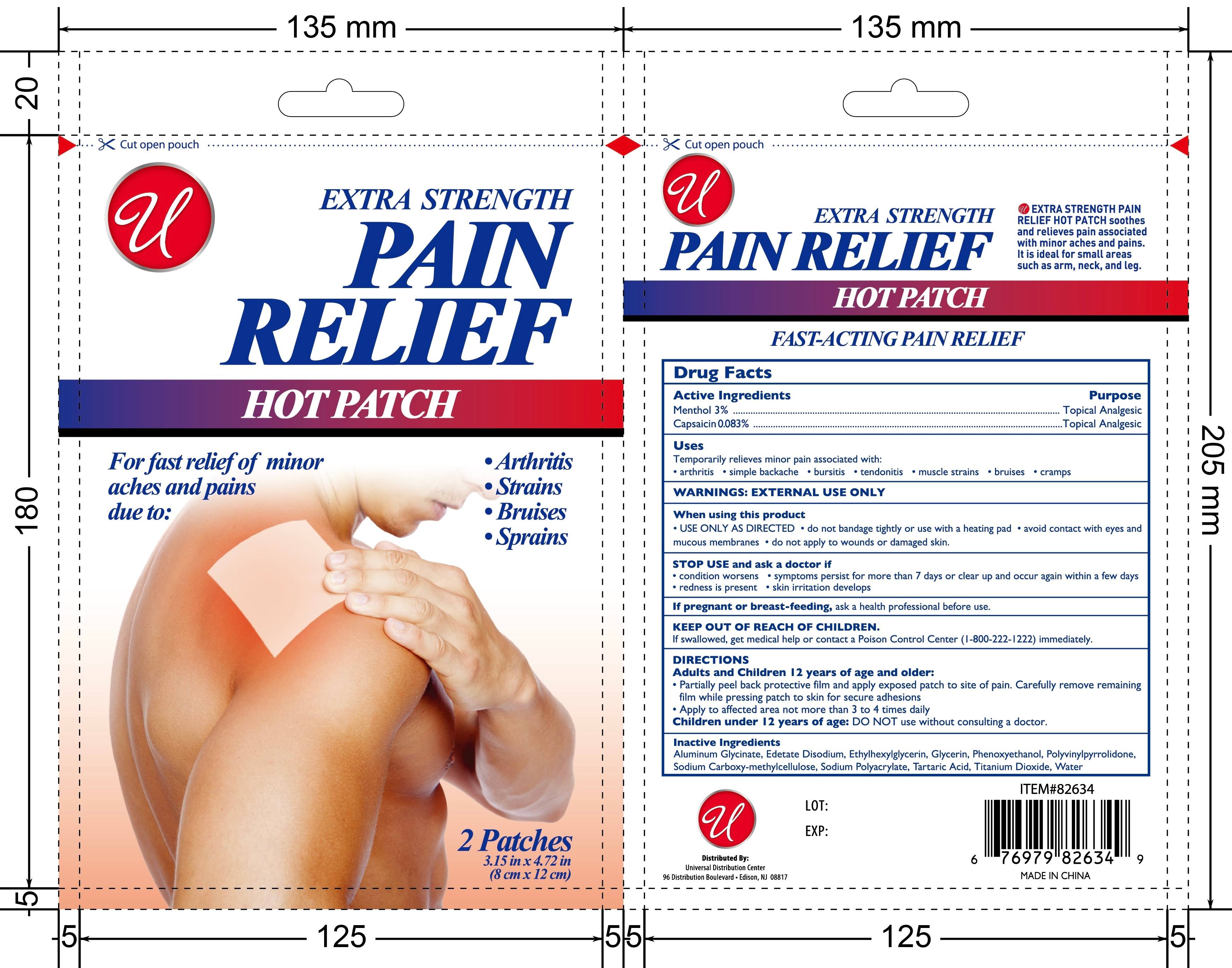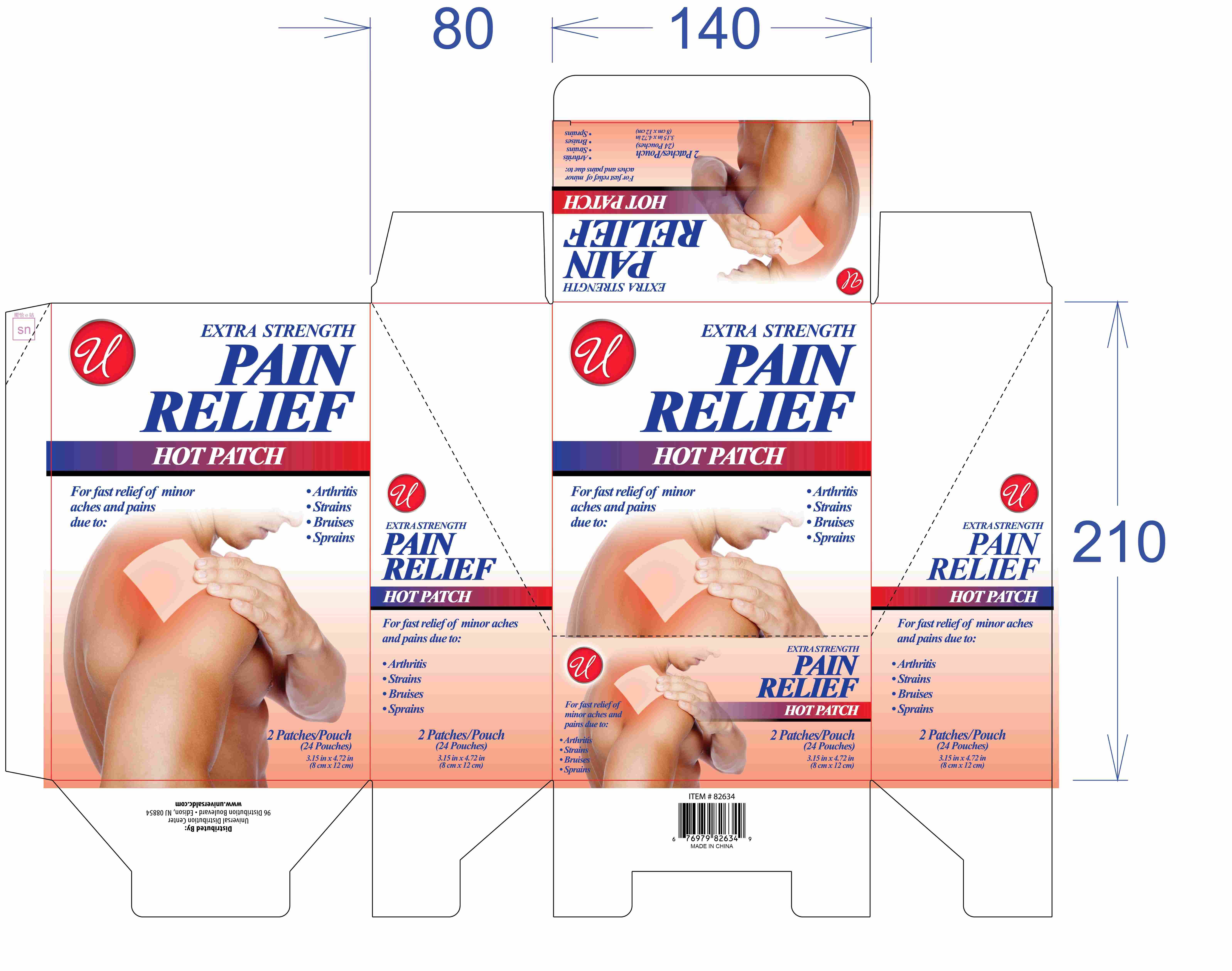 DRUG LABEL: PAIN RELIEF HOT Patch
NDC: 83559-016 | Form: PATCH
Manufacturer: Henan Enokon Medical Instrument Co., Ltd.
Category: otc | Type: HUMAN OTC DRUG LABEL
Date: 20260131

ACTIVE INGREDIENTS: MENTHOL 3 g/100 1; CAPSAICIN 0.083 g/100 1
INACTIVE INGREDIENTS: EDETATE DISODIUM; ETHYLHEXYLGLYCERIN; PHENOXYETHANOL; POVIDONE K90; DIHYDROXYALUMINUM AMINOACETATE ANHYDROUS; GLYCERIN; SODIUM POLYACRYLATE (2500000 MW); WATER; CARBOXYMETHYLCELLULOSE SODIUM, UNSPECIFIED; TARTARIC ACID; TITANIUM DIOXIDE

83559-016

Active Ingredient

Menthol 3%
Capsaicin 0.083%

Purpose

Topical Analgesic

Use

Temporarily relieves minor pain associated with:

arthritis • simple backache • bursitis • tendonitis • muscle strains • bruises • cramps

Warnings

EXTERNAL USE ONLY

When Using

• USE ONLY AS DIRECTED • do not bandage tightly or use with a heating pad • avoid contact with eyes and mucous membranes • do not apply to wounds or damaged skin.

Stop Use

STOP USE and ask a doctor if • condition worsens • symptoms persist for more than 7 days or clear up and occur again within a few days
• redness is present • skin irritation develops

Ask Doctor

If pregnant or breast-feeding, ask a health professional before use.

Keep Out Of Reach Of Children

If swallowed, get medical help or contact a Poison Control Center (1-800-222-1222) immediately.

Directions

Adults and Children 12 years of age and older:
• Partially peel back protective film and apply exposed patch to site of pain. Carefully remove remaining film while pressing patch to skin for secure adhesions
• Apply to affected area not more than 3 to 4 times daily

Children under 12 years of age: DO NOT use without consulting a doctor.

Other information

For fast relief of minor aches and pains due to:
• Arthritis
• Strains
• Bruises
• Sprains

EXTRA STRENGTH PAIN RELIEF HOT PATCH soothes and relieves pain associated with minor aches and pains. It is ideal for small areas such as arm, neck and leg.

FAST-ACTING PAIN RELIEF

Distributed by:
Universal Distribution Center
96 Distribution Boulevard • Edison, NJ 08817

MADE IN CHINA

Inactive ingredients

Aluminum Glycinate, Edetate Disodium, Ethylhexylglycerin, Glycerin, Phenoxyethanol, Polyvinylpyrrolidone, Sodium Carboxy-methylcellulose, Sodium Polyacrylate, Tartaric Acid, Titanium Dioxide, Water